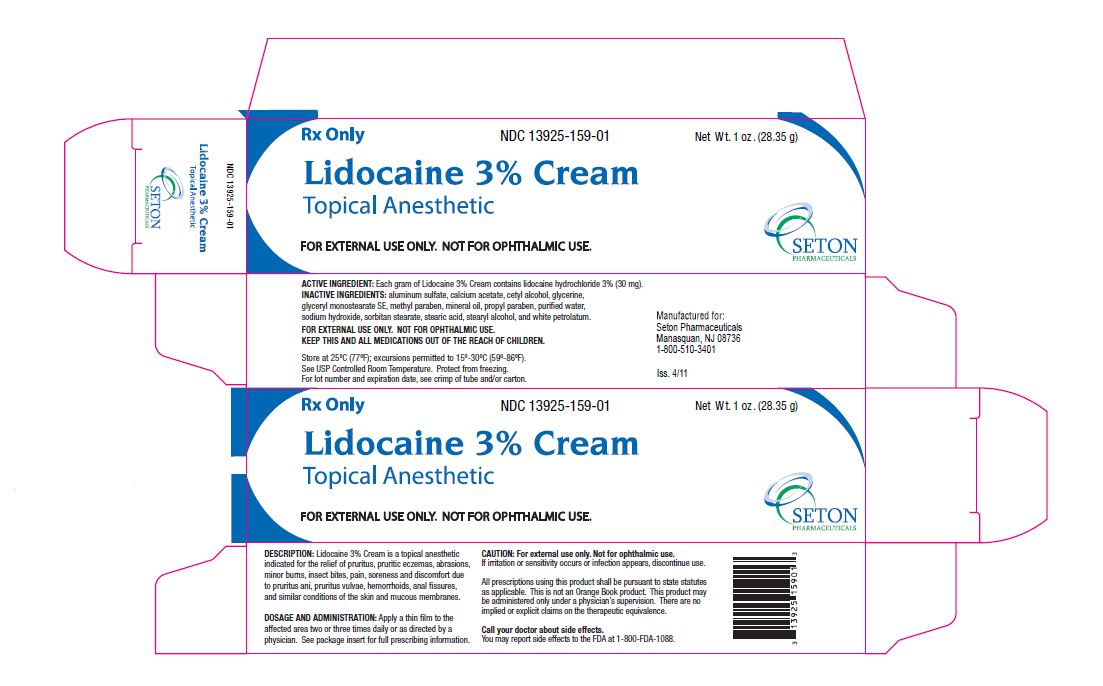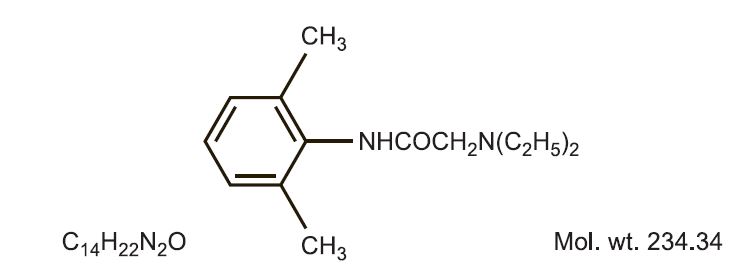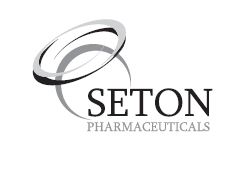 DRUG LABEL: Lidocaine Hydrochloride
NDC: 13925-159 | Form: CREAM
Manufacturer: Seton Pharmaceuticals
Category: prescription | Type: HUMAN PRESCRIPTION DRUG LABEL
Date: 20240130

ACTIVE INGREDIENTS: LIDOCAINE HYDROCHLORIDE 30 mg/1 g
INACTIVE INGREDIENTS: ALUMINUM SULFATE; CALCIUM ACETATE; CETYL ALCOHOL; GLYCERIN; GLYCERYL MONOSTEARATE; METHYLPARABEN; MINERAL OIL; PROPYLPARABEN; WATER; SODIUM HYDROXIDE; SORBITAN MONOSTEARATE; STEARIC ACID; STEARYL ALCOHOL; PETROLATUM

Lidocaine 3% Cream

Rx Only

DESCRIPTION:

Lidocaine 3% Cream is a topical anesthetic indicated for the relief of pruritus, pruritic eczemas, abrasions, minor burns, insect bites, pain, soreness, and discomfort due to pruritus ani, pruritus vulvae, hemorrhoids, anal fissures, and similar conditions of the skin and mucous membranes.

ACTIVE INGREDIENT:

Each gram of Lidocaine 3% Cream contains lidocaine hydrochloride 3% (30 mg).

INACTIVE INGREDIENTS:

aluminum sulfate, calcium acetate, cetyl alcohol, citric acid, glyceryl stearate (and) PEG-100 stearate, methylparaben, mineral oil, PEG-150 distearate, petrolatum, polycarbophil, propylene glycol, propylparaben, purified water, sodium citrate, sodium hydroxide, stearyl alcohol, xanthan gum.

CLINICAL PHARMACOLOGY:

MECHANISM OF ACTION:

Lidocaine 3% Cream releases lidocaine from a mild acidic vehicle to stabilize the neuronal membrane by inhibiting the ionic fluxes required for initiation and conduction of impulses, thereby effecting local anesthetic action. A mild acidic vehicle lowers pH to increase protection against alkaline irritations and to provide a favorable environment for healing.

Lidocaine is chemically designated as acetamide, 2- (diethylamino)-N-(2,6-dimethylphenyl), and has the following structure.

PHARMACOKINETICS:

Lidocaine may be absorbed following topical administration to mucous membranes, its rate and extent of absorption depending upon the specific site of application, duration of exposure, concentration and total dosage. In general, the rate of absorption of local anesthetic agents following topical application occurs most rapidly after intratracheal administration. Lidocaine is also well-absorbed from the gastrointestinal tract, but little intact drug appears in the circulation because of biotransformation in the liver.

Lidocaine is metabolized rapidly by the liver and metabolites and unchanged drug are excreted by the kidneys. Biotransformation includes oxidative N-dealkylation, ring hydroxylation, cleavage of the amide linkage and conjugation. N-dealkylation, a major pathway of biotransformation, yields the metabolites monoethylglycinexylidide and glycinexylidide. The pharmacological/ toxicological actions of these metabolites are similar to, but less potent than, those of lidocaine. Approximately 90% of lidocaine administered is excreted in the form of various metabolites and less than 10% is excreted unchanged. The primary metabolite in urine is a conjugate of 4-hydroxy-2, 6-dimethylaniline. The plasma binding of lidocaine is dependent on drug concentration, and the fraction bound decreases with increasing concentration. At concentrations of 1 to 4 g of free base per mL, 60 to 80 percent of lidocaine is protein bound. Binding is also dependent on the plasma concentration of the alpha-1-acid glycoprotein. Lidocaine crosses the blood-brain and placental barriers, presumably by passive diffusion. Studies of lidocaine metabolism following intravenous bolus injections have shown that the elimination half-life of this agent is typically 1.5 to 2 hours. Because of the rapid rate at which lidocaine is metabolized, any condition that affects liver function may alter lidocaine kinetics. The half-life may be prolonged two-fold or more in patients with liver dysfunction. Renal dysfunction does not affect lidocaine kinetics, but may increase the accumulation of metabolites. Factors such as acidosis and the use of CNS stimulants and depressants affect the CNS levels of lidocaine required to produce overt systemic effects. Objective adverse manifestations become increasingly apparent with increasing venous plasma levels above 6 g free base per mL. In the rhesus monkey, arterial blood levels of 18-21 g/mL have been shown to be threshold for convulsive activity.

INDICATIONS:

Anesthetic for relief of pruritus, pruritic eczemas, abrasions, minor burns, insect bites, pain, soreness and discomfort due to pruritus ani, pruritus vulvae, hemorrhoids, anal fissures, and similar conditions of the skin and mucous membranes.

CONTRAINDICATIONS:

Traumatized mucosa, secondary bacterial infection of the area of proposed application and known hypersensitivity to any of the components. Lidocaine is contraindicated in patients with a known history of hypersensitivity to local anesthetics of the amide type.

WARNINGS:

For external use only. Not for ophthalmic use.

Methemoglobinemia

Cases of methemoglobinemia have been reported in association with local anesthetic use. Although all patients are at risk for methemoglobinemia, patients with glucose-6-phosphate dehydrogenase deficiency, congenital or idiopathic methemoglobinemia, cardiac or pulmonary compromise, infants under 6 months of age, and concurrent exposure to oxidizing agents or their metabolites are more susceptible to developing clinical manifestations of the condition. If local anesthetics must be used in these patients, close monitoring for symptoms and signs of methemoglobinemia is recommended.

Signs and symptoms of methemoglobinemia may occur immediately or may be delayed some hours after exposure and are characterized by a cyanotic skin discoloration and abnormal coloration of the blood. Methemoglobin levels may continue to rise; therefore, immediate treatment is required to avert more serious central nervous system and cardiovascular adverse effects, including seizures, coma, arrhythmias, and death. Discontinue [the use of this product] and any other oxidizing agents. Depending on the severity of the symptoms, patients may respond to supportive care, i.e., oxygen therapy, hydration. More severe symptoms may require treatment with methylene blue, exchange transfusion, or hyperbaric oxygen.

DRUG INTERACTIONS:

Patients that are administered local anesthetics may be at increased risk of developing methemoglobinemia when concurrently exposed to the following oxidizing agents:

Class | Examples
Nitrates/Nitrites | nitroglycerin, nitroprusside, nitric oxide, nitrous oxide
Local anesthetics | benzocaine, lidocaine, bupivacaine, mepivacaine, tetracaine, prilocaine, procaine, articaine, ropivacaine
Antieoplastic agents | cyclophosphamide, flutamide, rasburicase, ifosfamide, hydroxyurea
Antibiotics | dapsone, sulfonamides, nitrofurantoin, para-aminosalicyclic acid
Antimalarials | chloroquine, primaquine
Anticonvulsants | phenytoin, sodium valproate, phenobarbital
Other drugs | acetaminophen, metoclopramide, sulfa drugs (i.e., sulfasalazine), quinine

PATIENT COUNSELING INFORMATION:

Inform patients that use of local anesthetics may cause methemoglobinemia, a serious condition that must be treated promptly. Advise patients or caregivers to stop use and seek immediate medical attention if they or someone in their care experience the following signs or symptoms: pale, gray, or blue colored skin (cyanosis); headache; rapid heart rate; shortness of breath; lightheadedness; or fatigue.

PRECAUTIONS:

If irritation or sensitivity occurs or infection appears, discontinue use and institute appropriate therapy. Lidocaine 3% Cream should be used with caution in ill, elderly, debilitated patients and children who may be more sensitive to the systemic effects of lidocaine.

CARCINOGENESIS, MUTAGENESIS AND IMPAIRMENT OF FERTILITY:

Studies of lidocaine in animals to evaluate the carcinogenic and mutagenic potential of the effect on fertility have not been conducted.

USE IN PREGNANCY:

Teratogenic Effects; Pregnancy Category B:

Reproduction studies have been performed for lidocaine in rats at doses up to 6.6 times the human dose and have revealed no evidence of harm to the fetus caused by lidocaine. There are, however, no adequate and well-controlled studies in pregnant women. Animal reproduction studies are not always predictive of human response. General consideration should be given to this fact before administering lidocaine to women of childbearing potential, especially during early pregnancy when maximum organogenesis takes place.

NURSING MOTHERS:

Lidocaine is excreted in human milk. The clinical significance of this observation is unknown. Caution should be exercised when lidocaine is administered to a nursing woman.

PEDIATRIC USE:

Dosage in pediatric patients should be reduced commensurate with age, body weight and physical condition.

ADVERSE REACTIONS:

During or immediately after treatment, the skin at the site of treatment may develop erythema or edema or may be the locus of abnormal sensation.

Call your doctor about side effects. You may report side effects to the FDA at 1-800-FDA-1088.

DOSAGE AND ADMINISTRATION:

Apply a thin film to the affected area two or three times daily or as directed by a physician.

HOW SUPPLIED:

Lidocaine 3% Cream is supplied as a white cream in:

1 oz. (28.35 g) tubes, NDC 13925-159-01

3 oz. (85 g) tubes, NDC 13925-159-03

STORAGE AND HANDLING SECTION

KEEP THIS AND ALL MEDICATIONS OUT OF THE REACH OF CHILDREN.

All prescriptions using this product shall be pursuant to state statutes as applicable. This is not an Orange Book product. This product may be administered only under a physician’s supervision. There are no implied or explicit claims on the therapeutic equivalence.

Store at 25ºC (77ºF); excursions permitted to 15º-30ºC (59º-86º F). See USP Controlled Room Temperature. Protect from freezing.

Marketed by:

Seton Pharmaceuticals

Manasquan, NJ 08736

1-800-510-3401

Iss. 01/19

1900008

PACKAGE LABEL.PRINCIPAL DISPLAY PANEL

Rx Only NDC-13925-159-01 Net Wt. 1 oz. (28.35 g)

Lidocaine 3% Cream
Topical Anesthetic

FOR EXTERNAL USE ONLY. NOT FOR OPHTHALMIC USE.

SETON PHARMACEUTICALS